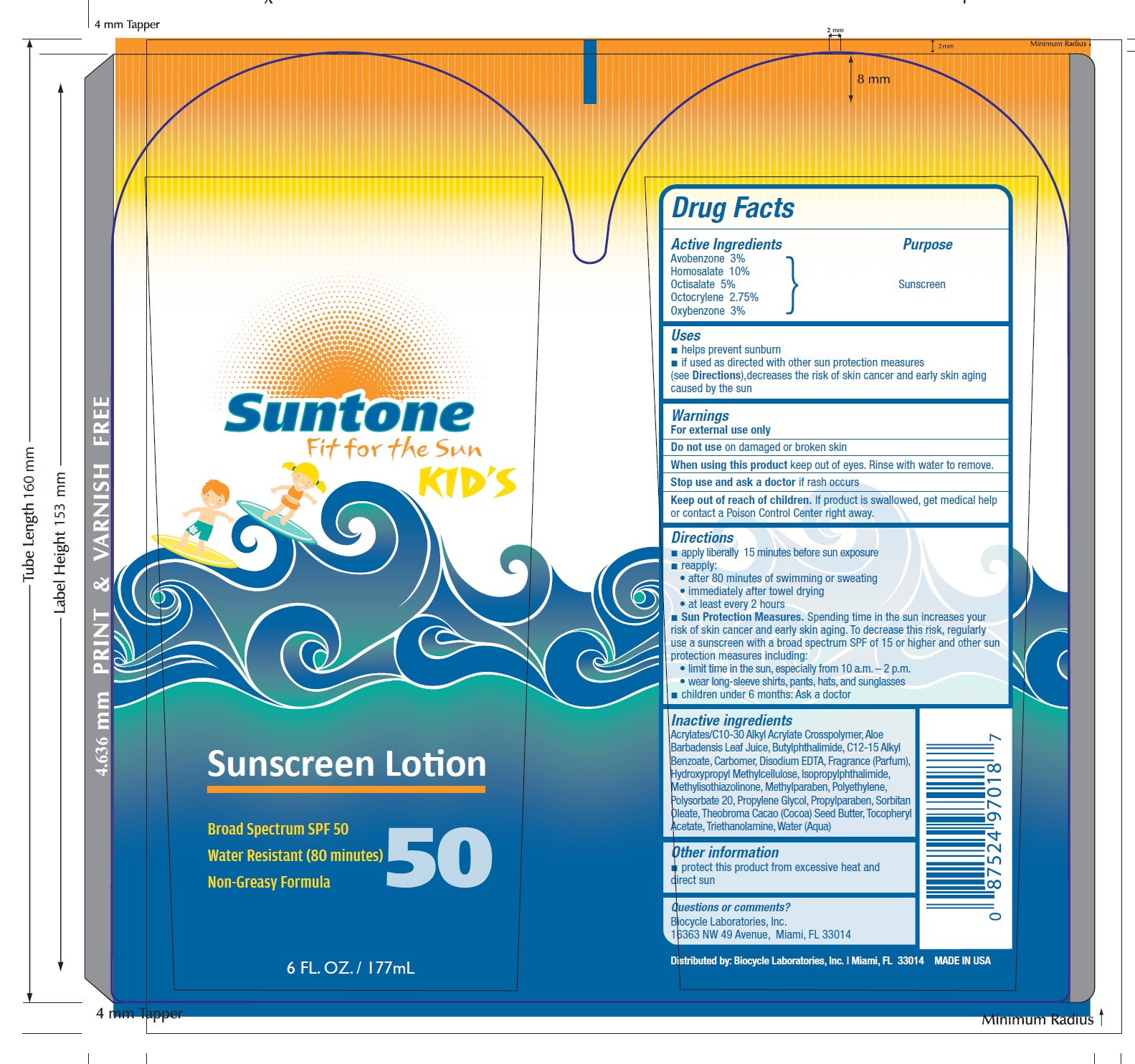 DRUG LABEL: Suntone
NDC: 58443-0138 | Form: LOTION
Manufacturer: Prime Enterprises Inc.
Category: otc | Type: HUMAN OTC DRUG LABEL
Date: 20200117

ACTIVE INGREDIENTS: AVOBENZONE 30 mg/1 mL; HOMOSALATE 100 mg/1 mL; OCTISALATE 50 mg/1 mL; OCTOCRYLENE 27.5 mg/1 mL; OXYBENZONE 30 mg/1 mL
INACTIVE INGREDIENTS: PROPYLPARABEN; ISOPROPYLPHTHALIMIDE; COCOA BUTTER; EDETATE DISODIUM; HYPROMELLOSES; HIGH DENSITY POLYETHYLENE; POLYSORBATE 20; PROPYLENE GLYCOL; SORBITAN MONOOLEATE; CARBOMER 940; ALKYL (C12-15) BENZOATE; ALOE VERA LEAF; (C10-C30)ALKYL METHACRYLATE ESTER; TROLAMINE; ALPHA-TOCOPHEROL ACETATE; WATER; N-BUTYLPHTHALIMIDE; METHYLISOTHIAZOLINONE; METHYLPARABEN

Suntone Kids Broad Spectrum SPF 50 Sunscreen

Active Ingredients

Avobenzone 3%

Homosalate 10%

Octisalate 5%

Octocrylene 2.75%

Oxybenzone 3%

Purpose

Sunscreen

Uses

- helps prevent sunburn
- if used as directed with other sun protection measures (see Directions), decreases the risk of skin cancer and early skin aging caused by the sun

Warnings

For external use only.

Do not use on damaged or broken skin

When using this product keep out of eyes. Rinse with water to remove.

Stop use and ask a doctor if rash occurs

Keep out of reach of children. If product is swallowed, get medical help or contact a Poison Control Center right away.

Directions

- apply liberally 15 minutes before sun exposure
- reapply:
- after 80 minutes of swimming or sweating
- immediately after towel drying
- at least every 2 hours
- Sun Protection Measures. Spending time in the sun increases your risk of skin cancer and early skin aging. To decrease this risk, regularly use a sunscreen with broad spectrum SPF of 15 or higher and other sun protection measures including:
- limit time in the sun, especially from 10 a.m. – 2 p.m.
- wear long-sleeve shirts, pants, hats, and sunglasses
- children under 6 months: Ask a doctor

INACTIVE INGREDIENT

Acrylates/C10-30 Alkyl Acrylate Crosspolymer, Aloe Barbadensis Leaf Juice, Butylphthalimide, C12-15 Alkyl Benzoate, Carbomer, Disodium EDTA, Fragrance (Parfum), Hydroxypropyl Methylcellulose, Isopropylphthalimide, Methylisothiazolinone, Methylparaben, Polyethylene, Polysorbate 20, Propylene Glycol, Propylparaben, Sorbitan Oleate, Theobroma Cacao (Cocoa) Seed Butter, Tocopheryl Acetate, Triethanolamine, Water (Aqua)

Other Information

- protect this product from excesive heat and direct sun

Questions or Comments?

Biocycle Laboratories. Inc.

16363 NW 49 Avenue, Miami, FL 33014